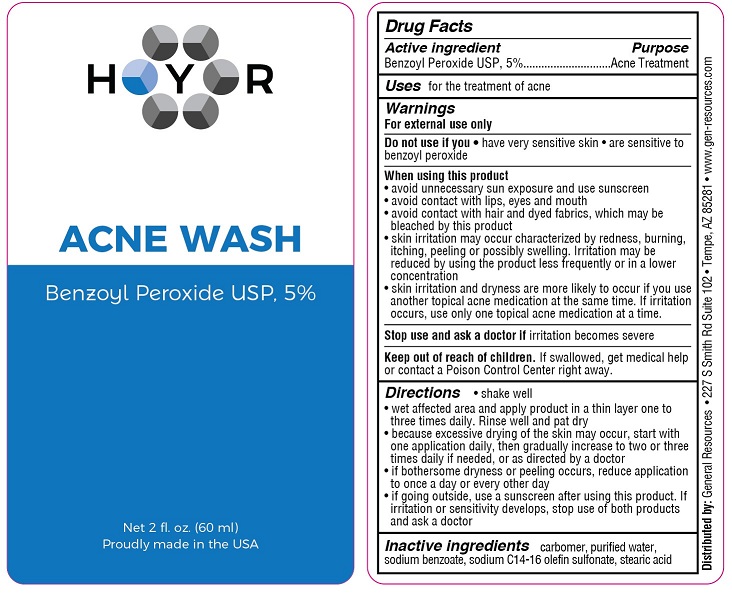 DRUG LABEL: HYR Acne Wash
NDC: 70481-330 | Form: SOLUTION
Manufacturer: General Resources LLC
Category: otc | Type: HUMAN OTC DRUG LABEL
Date: 20201018

ACTIVE INGREDIENTS: BENZOYL PEROXIDE 5 g/100 mL
INACTIVE INGREDIENTS: SODIUM C14-16 OLEFIN SULFONATE; WATER; SODIUM BENZOATE; STEARIC ACID; CARBOMER HOMOPOLYMER, UNSPECIFIED TYPE

HYR Acne Wash (Benzoyl Peroxide 5%)

Drug Facts

Active ingredient

Benzoyl Peroxide USP, 5%

Purpose

Acne Treatment

Uses
for the treatment of acne

Warnings

For external use only.

Do not use if you

- have very sensitive skin
- are sensitive to benzoyl peroxide

When using this product

- avoid unnecessary sun exposure and use a sunscreen
- avoid contact with eyes, lips and mouth
- avoid contact with hair and dyed fabrics, which may be bleached by this product
- skin irritation may occur, characterized by redness, burning, itching, peeling, or possibly swelling. Irritation may be reduced by using the product less frequently or in a lower concentration
- skin irritation and dryness is more likely to occur if you use another topical acne medication at the same time. If irritation occurs, only use one topical acne medication at a time.

Stop use and ask a doctor if irritation becomes severe

KEEP OUT OF REACH OF CHILDREN

Keep out of the reach of children. If swallowed, get medical help or contact a Poison Control Center right away.

Directions

- shake well
- wet affected area and apply product in a thin layer one to three times daily. Rinse well and pat dry.
- because excessive drying of the skin may occur, start with one application daily, then gradually increase to two or three times daily if needed or directed by a doctor.
- if bothersome dryness or peeling occurs, reduce application to once a day or every other day
- if going outside, use a sunscreen after using this product. If irritation or sensitivity develops, stop use of both products and ask a doctor.

INACTIVE INGREDIENT

Inactive ingredients carbomer, purified water, sodium benzoate, sodium C14-16 olefin sulfonate, stearic acid

Distributed by: General Resources • 227 S Smith Rd Suite 102 • Tempe, AZ 85281 • www.gen-resources.com

PACKAGE LABEL

HYR

ACNE WASH

Benzoyl Peroxide USP, 5%

Net 2 fl oz (60 ml)

Proudly made in the USA